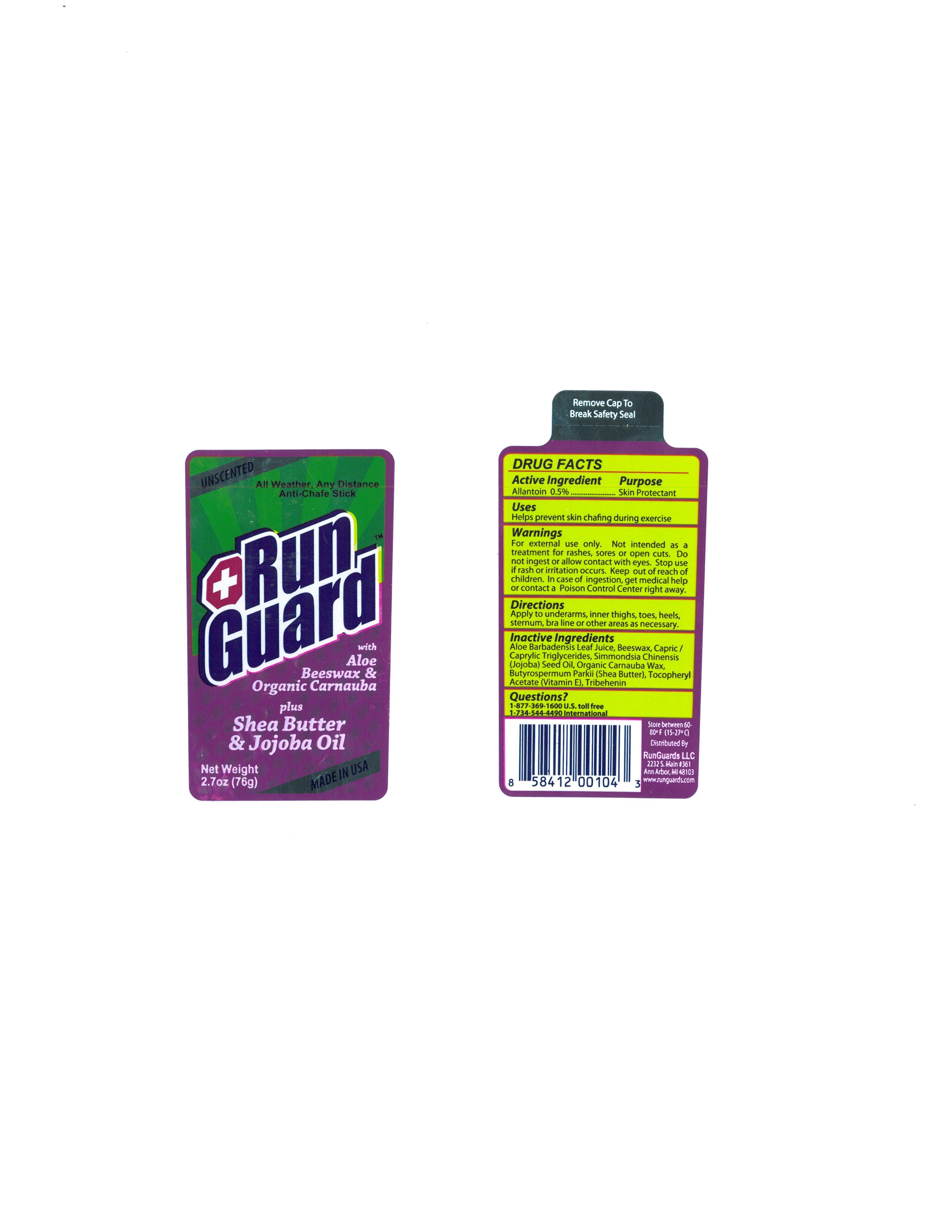 DRUG LABEL: Run Guard Sensitive
NDC: 24474-002 | Form: STICK
Manufacturer: RunGuards LLC
Category: otc | Type: HUMAN OTC DRUG LABEL
Date: 20140902

ACTIVE INGREDIENTS: ALLANTOIN 0.5 g/100 g
INACTIVE INGREDIENTS: ALOE VERA LEAF; YELLOW WAX; MEDIUM-CHAIN TRIGLYCERIDES; JOJOBA OIL; CARNAUBA WAX; SHEA BUTTER; .ALPHA.-TOCOPHEROL ACETATE; TRIBEHENIN

Drug Facts

Active Ingredient

Allantoin 0.5%

Purpose

Skin Protectant

Uses

Helps prevent skin chafing during exercise

Warnings

For external use only.

Not intended as a treatment for rashes, sores or open cuts. Do not ingest or allow contact with eyes. Stop use if rash or irritation occurs.

Keep out of reach of children.

In case of ingestion, get medical help or contact a Poison Control Center right away.

Directions

Apply to underarms, inner thighs, toes, heels, sternum, bra line or other areas as necesssary.

Inactive Ingredients

Aloe Barbadensis Leaf Juice, Beeswax, Capric/Caprylic Triglycerides, Simmondsia Chinensis (Jojoba) Seed Oil, Organic Carnauba Wax, Butyrospermum Parkii (Shea Butter), Tocopheryl Acetate (Vitamin E), Tribehenin

Questions?

1-877-369-1600 U.S. toll free

1-734-544-4490 International

PACKAGE LABEL

UNSCENTED

All Weather, Any Distance

Ant-Chafe Stick

*Run

Guard

with Aloe

Beeswax and

Organic Carnauba

plus Shea Butter

and Jojoba Oil

Net Weight

2.7 oz (76g)

MADE IN USA